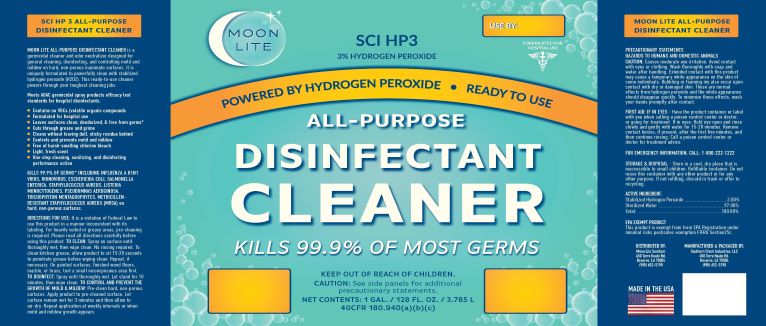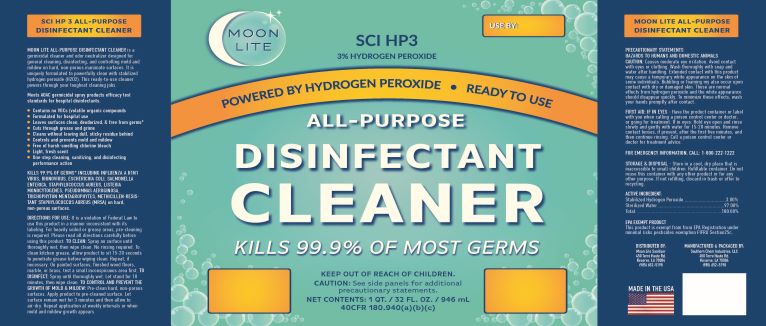 DRUG LABEL: Surface Cleaner
NDC: 55549-301 | Form: LIQUID
Manufacturer: Southern Chem Industries LLC
Category: otc | Type: HUMAN OTC DRUG LABEL
Date: 20210323

ACTIVE INGREDIENTS: HYDROGEN PEROXIDE 3 mL/100 mL
INACTIVE INGREDIENTS: WATER

HP3

1. Citric Acid
2. Lemon Grass Extract
3. Water
4. Quillaja Saponin (Soap Bark)
5. Stearic Acid

Active Ingredient(s)

Hydrogen Peroxide

Purpose

Surface Cleaner

Use

For surface cleaning to decrease bacteria.

Warnings

DO NOT CONSUME

Keep out of reach of children. If swallowed, get medical help or contact a Poison Control Center right away.

Other information

Store in a cool, dry area, out of reach of children

Inactive ingredients

Water

EPA Excempt Product

This Product is excempt from the EPA Registration under minimal risk pesticide exception FIFRA Section 25c

Directions

Apply as needed to cover area targeted for antimicrobial cleansing application.